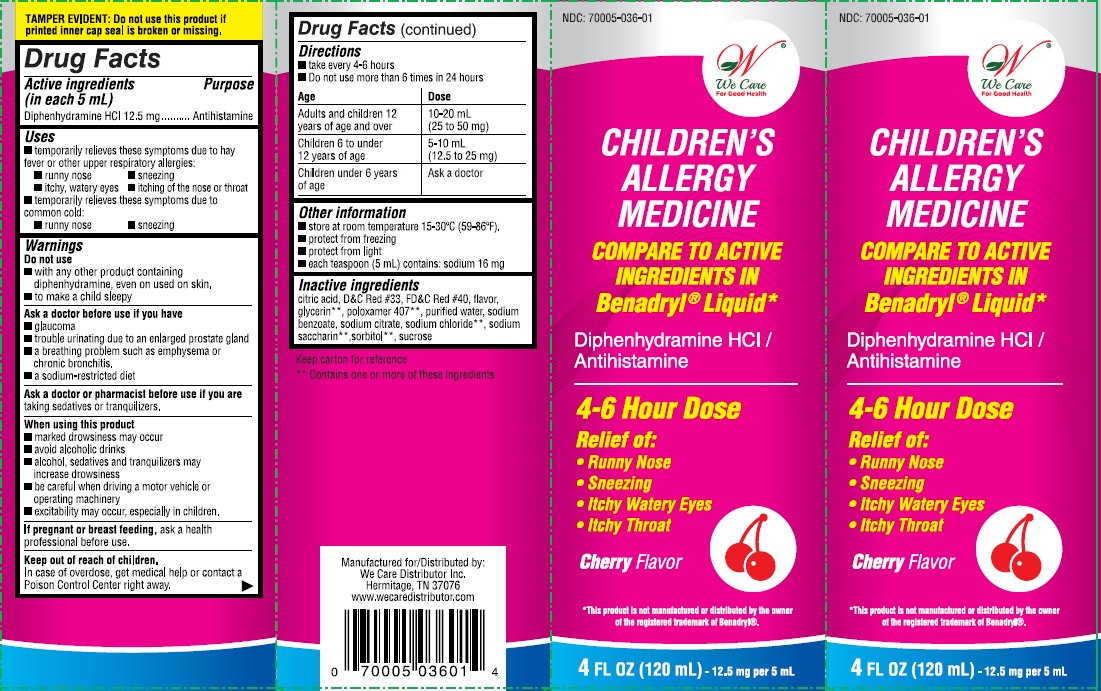 DRUG LABEL: Allergy
NDC: 70005-036 | Form: LIQUID
Manufacturer: We Care Distributors Inc.
Category: otc | Type: HUMAN OTC DRUG LABEL
Date: 20160816

ACTIVE INGREDIENTS: DIPHENHYDRAMINE HYDROCHLORIDE 12.5 mg/5 mL
INACTIVE INGREDIENTS: ANHYDROUS CITRIC ACID; D&C RED NO. 33; FD&C RED NO. 40; GLYCERIN; HIGH FRUCTOSE CORN SYRUP; POLOXAMER 407; WATER; SODIUM BENZOATE; SODIUM CHLORIDE; SODIUM CITRATE; SACCHARIN SODIUM; SUCROSE; SORBITOL

We Care Allergy Drug Facts

Active ingredient (in each 5 mL)*

Diphenhydramine HCl 12.5 mg

*5 mL = 1 teaspoon (tsp)

Purpose

Antihistamine

Uses

- temporarily relieves these symptoms due to hay fever or other upper respiratory allergies:
- runny nose
- sneezing
- itchy, watery eyes
- itching of the nose or throat
- temporarily relieves these symptoms due to common cold:
- runny nose
- sneezing

Warnings

Do not use

- with any other product containing diphenhydramine, even one used on skin
- to make a child sleepy

Ask a doctor before use if you have

- glaucoma
- trouble urinating due to an enlarged prostate gland
- a breathing problem such as emphysema or chronic bronchitis
- a sodium-restricted diet

Ask a doctor or pharmacist before use if you are

taking sedatives or tranquilizers

When using this product

- marked drowsiness may occur
- avoid alcoholic drinks
- alcohol, sedatives or tranquilizers may increase drowsiness
- be careful when operating a motor vehicle or operating machinery
- excitability may occur especially in children

If pregnant or breast-feeding

ask a health professional before use.

Keep out of reach of children.

In case of overdose, get medical help or contact a Poison Control Center right away. (1-800-222-1222)

Directions

- take every 4 - 6 hours
- do not take more than 6 times in 24 hours

Age (yr) | Dose
Adult and children 12; years of age and over | 10-20 mL; (25 to 50 mg)
Children 6 to under; 12 years of age | 5-10 mL; (12.5 to 25 mg)
Children under 6 years; of age | Ask a doctor

Other information

- store at room temperature 15-30°C (59-86°F)
- protect from freezing
- protect from light
- each teaspoon (5 mL) contains: sodium 16 mg

Inactive ingredients

citric acid, D&C red #33, FD&C red #40, flavor, glycerin, high fructose corn syrup, poloxamer 407, purified water, sodium benzoate, sodium chloride, sodium citrate, sodium sacchrin, sorbitol, sucrose

Questions or comments?

1-888-705-WECARE (Mon-Fri 9am-5pm EST) or www.wecaredistributor.com

Principal Display Panel

Compare to the active ingredient in Children’s Benadryl® Allergy Liquid

See New Warnings and Directions

CHILDREN'S ALLERGY

LIQUID MEDICATION

DIPHENHYDRAMINE HCl

ORAL SOLUTION

ANTIHISTAMINE

Relieves: Sneezing, Runny nose, Itchy, watery eyes, Itchy throat

Cherry Flavored

Alcohol Free